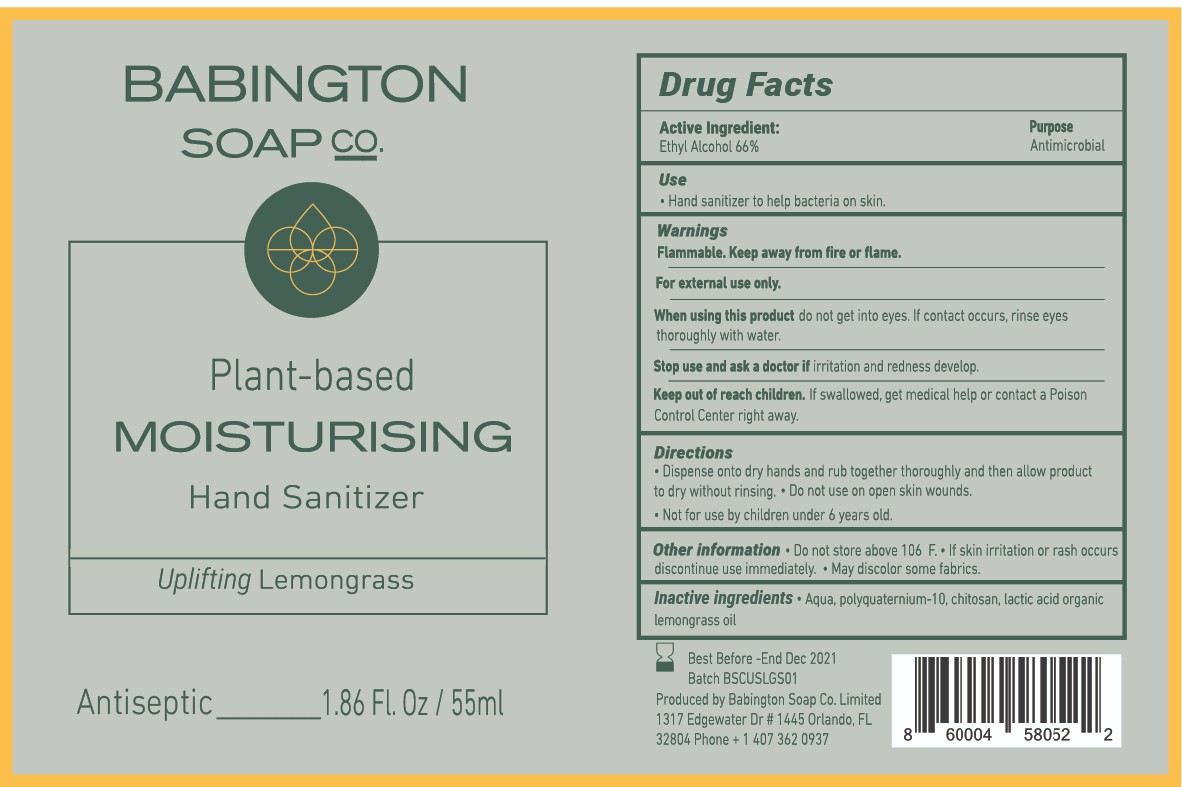 DRUG LABEL: BabingtonSoapCo
NDC: 80104-111 | Form: GEL
Manufacturer: Babington Soap Co Limited
Category: otc | Type: HUMAN OTC DRUG LABEL
Date: 20201202

ACTIVE INGREDIENTS: ALCOHOL 66 mL/100 mL
INACTIVE INGREDIENTS: POLYQUATERNIUM-10 (20000 MPA.S AT 2%); CYMBOPOGON SCHOENANTHUS OIL; WATER; LACTIC ACID; CHITOSAN MEDIUM MOLECULAR WEIGHT (200-400 MPA.S)

Babington Soap Co. 55ML

Active Ingredient(s)

Alcohol 66% v/v. Purpose: Antiseptic

Purpose

Antiseptic, Hand Sanitizer

Use

Hand Sanitizer to help reduce bacteria on the skin.

Warnings

Flammable. Keep away from fire or flame

For external use only.

When using this product keep out of eyes, ears, and mouth. In case of contact with eyes, rinse eyes thoroughly with water.
Stop use and ask a doctor if irritation and redness develop.
Keep out of reach of children. If swallowed, get medical help or contact a Poison Control Center right away.

Stop use and ask a doctor if irritation and redness develop.

Keep out of reach of children. If swallowed, get medical help or contact a Poison Control Center right away.

Directions

- Dispense onto dry hands and rub together thoroughly and then allow product to dry without rinsing. Do not use on open skin or wounds.
- Not for use by children under 6 years old.

Other information

- Do not store above 106F.
- If skin irritation or rash occurs discontinue use immediately.
- May discolor some fabrics.

Inactive ingredients

Aqua, Polyquaternium 10, Chitosan, lactic acid organic, lemongrass oil.

Package Label - Principal Display Panel

55 mL NDC: 80104-111-11